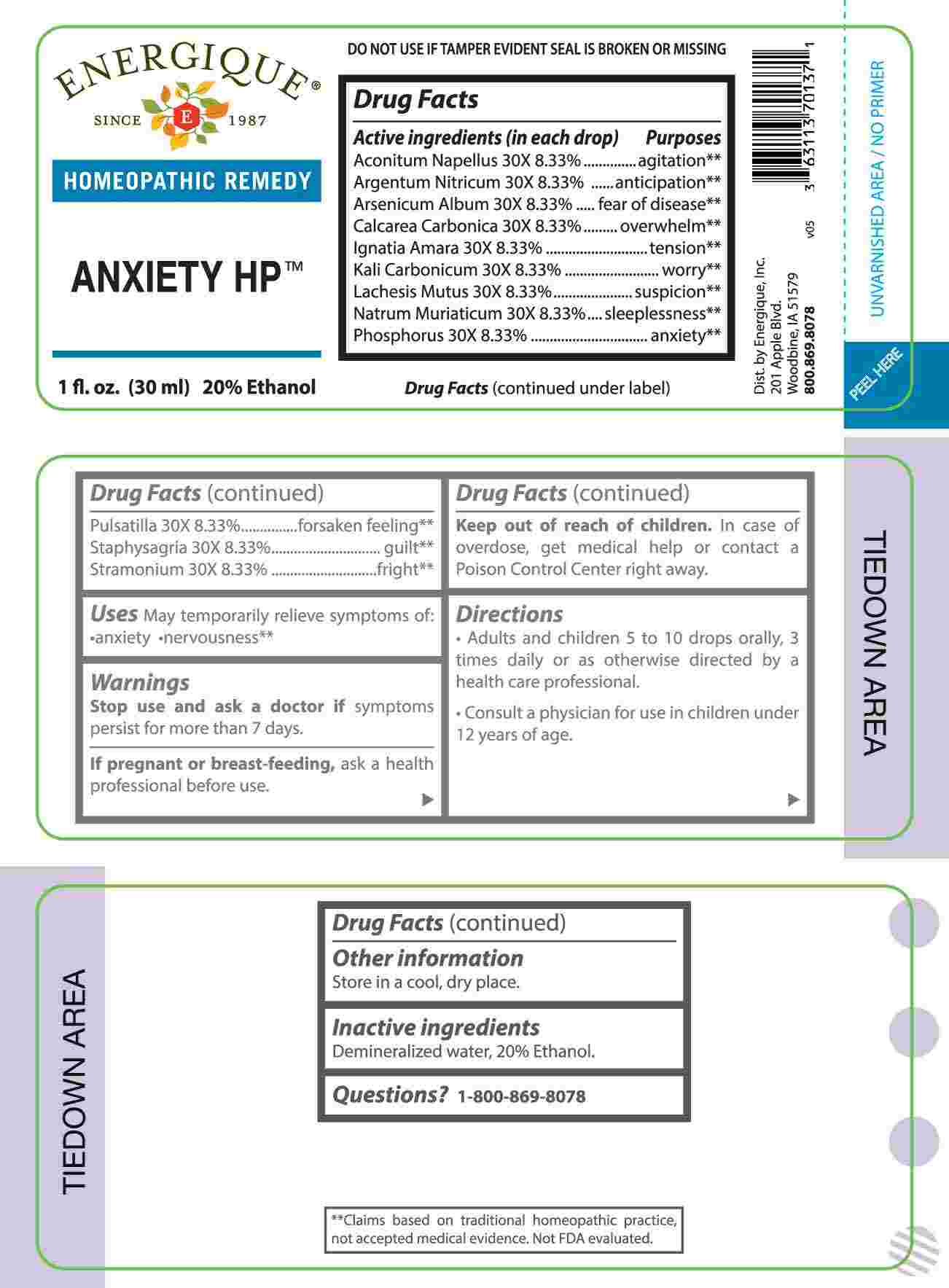 DRUG LABEL: Anxiety
NDC: 44911-0675 | Form: LIQUID
Manufacturer: Energique, Inc.
Category: homeopathic | Type: HUMAN OTC DRUG LABEL
Date: 20250320

ACTIVE INGREDIENTS: ACONITUM NAPELLUS WHOLE 30 [hp_X]/1 mL; SILVER NITRATE 30 [hp_X]/1 mL; ARSENIC TRIOXIDE 30 [hp_X]/1 mL; OYSTER SHELL CALCIUM CARBONATE, CRUDE 30 [hp_X]/1 mL; STRYCHNOS IGNATII SEED 30 [hp_X]/1 mL; POTASSIUM CARBONATE 30 [hp_X]/1 mL; LACHESIS MUTA VENOM 30 [hp_X]/1 mL; SODIUM CHLORIDE 30 [hp_X]/1 mL; PHOSPHORUS 30 [hp_X]/1 mL; PULSATILLA PRATENSIS WHOLE 30 [hp_X]/1 mL; DELPHINIUM STAPHISAGRIA SEED 30 [hp_X]/1 mL; DATURA STRAMONIUM 30 [hp_X]/1 mL
INACTIVE INGREDIENTS: WATER; ALCOHOL

DRUG FACTS:

ACTIVE INGREDIENTS:

(in each drop) Aconitum Napellus 30X 8.33%, Argentum Nitricum 30X 8.33%, Arsenicum Album 30X 8.33%, Calcarea Carbonica 30X 8.33%, Ignatia Amara 30X 8.33%, Kali Carbonicum 30X 8.33%, Lachesis Mutus 30X 8.33%, Natrum Muriaticum 30X 8.33%, Phosphorus 30X 8.33%, Pulsatilla 30X 8.33%, Staphysagria 30X 8.33%, Stramonium 30X 8.33%.

PURPOSE:

Aconitum Napellus – agitation,** Argentum Nitricum - anticipation,** Arsenicum Album – fear of disease,** Calcarea Carbonica - overwhelm,** Ignatia Amara - tension,** Kali Carbonicum - worry,** Lachesis Mutus - suspicion,** Natrum Muriaticum - sleeplessness,** Phosphorus - anxiety,** Pulsatilla – forsaken feeling,** Staphysagria - guilt,** Stramonium - fright.**

**Claims based on traditional homeopathic practice, not accepted medical evidence. Not FDA evaluated.

USES:

May temporarily relieve symptoms of: •anxiety nervousness. **

**Claims based on traditional homeopathic practice, not accepted medical evidence. Not FDA evaluated.

WARNINGS:

Stop use and ask a doctor if symptoms persist for more than 7 days.

If pregnant or breast-feeding, ask a health professional before use.

Keep out of reach of children. In case of overdose, get medical help or contact a Poison Control Center right away.

DO NOT USE IF TAMPER EVIDENT SEAL IS BROKEN OR MISSING

Store in a cool, dry place.

KEEP OUT OF REACH OF CHILDREN:

In case of overdose, get medical help or contact a Poison Control Center right away.

DIRECTIONS:

• Adults and children 5 to 10 drops orally, 3 times daily or as otherwise directed by a health care professional.

• Consult a physician for use in children under 12 years of age.

INACTIVE INGREDIENTS:

Demineralized water, 20% Ethanol.

QUESTIONS:

Dist. by Energique, Inc.

201 Apple Blvd.

Woodbine, IA 51579

800-869-8078

PACKAGE LABEL DISPLAY:

ENERGIQUE

SINCE 1987

HOMOEPATHIC REMEDY

ANXIETY HP

1 fl. oz. (30 ml)